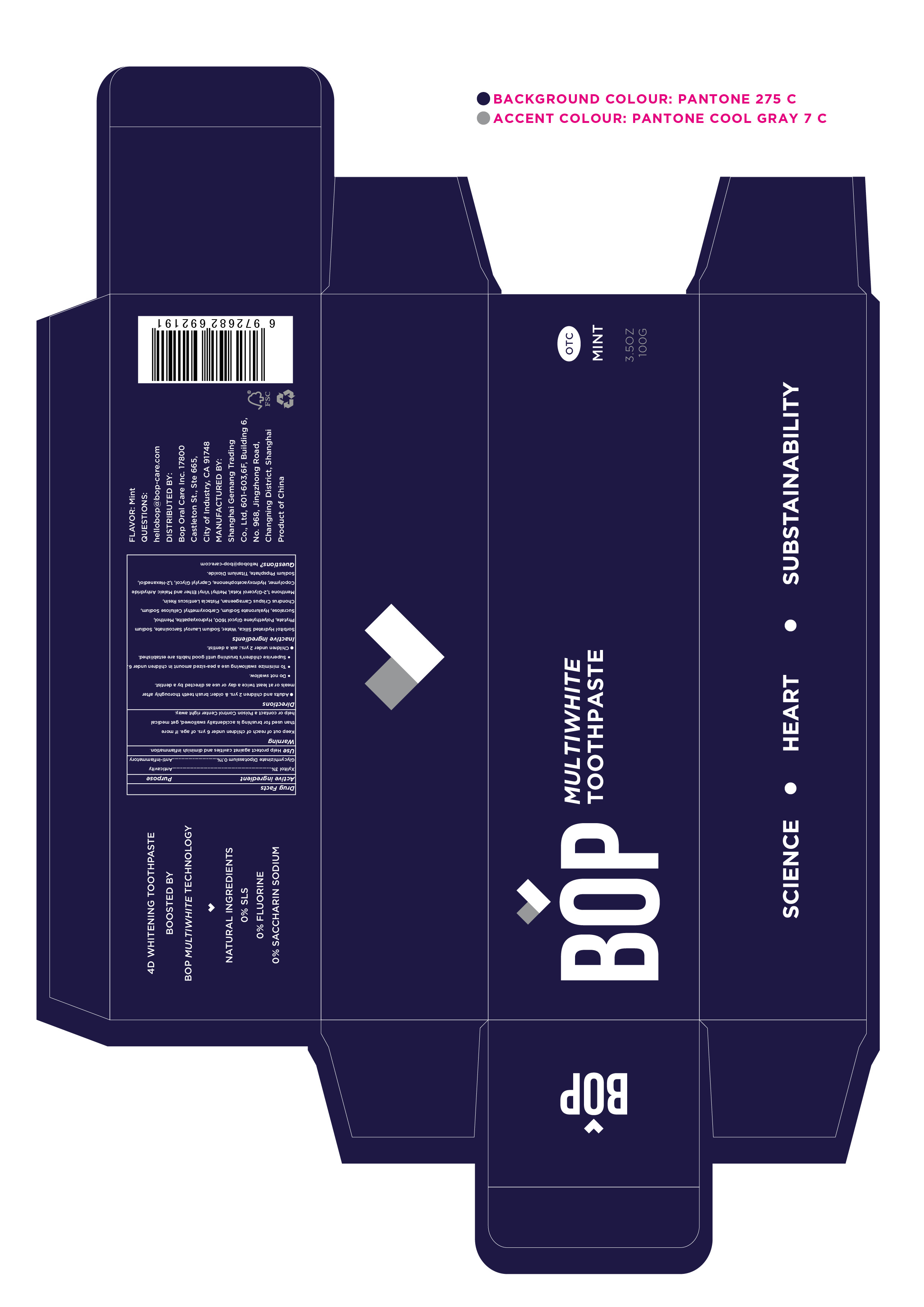 DRUG LABEL: BOP whiteningtoothpaste
NDC: 82574-001 | Form: GEL
Manufacturer: Shanghai Gemang Trading Co., Ltd.
Category: otc | Type: HUMAN OTC DRUG LABEL
Date: 20220222

ACTIVE INGREDIENTS: GLYCYRRHIZINATE DIPOTASSIUM 0.3 g/100 g; XYLITOL 3 g/100 g
INACTIVE INGREDIENTS: SODIUM PHOSPHATE; PHYTATE SODIUM; POLYETHYLENE GLYCOL 1600; TRIBASIC CALCIUM PHOSPHATE; 5-METHYL-1,3,5-TRIPHENYL-2-PYRAZOLINE; HYALURONATE SODIUM; PISTACIA LENTISCUS RESIN; MENTHONE 1,2-GLYCEROL KETAL, (+/-)-; HYDROXYACETOPHENONE; 1,2-HEXANEDIOL; SORBITOL; HYDRATED SILICA; WATER; SODIUM LAUROYL SARCOSINATE; MENTHOL; CHONDRUS CRISPUS CARRAGEENAN; CAPRYLYL GLYCOL; TITANIUM DIOXIDE

ACTIVE INGREDIENT

XYLITOL

GLYCYRRHIZINATE DIPOTASSIUM

INACTIVE INGREDIENT

Sorbitol Hydrated silica, Water, Sodium Lauroyl Sarcosinate,Sodium Phytate, Polyethylene Glycol 1600,Hydroxyapatite,Menthol,

sucralose,Hyaluronate Sodium,Chondrus Crispus Carrageenan,Pistacia Lentiscus Resin,Menthone 1,2-Glycerol

Ketal,Hydroxyacetophenone, Caprylyl Glycol,1,2-Hexanediol,Sodium Phpsphate,Titanium Dioxide.

Keep out of reach of children under 6 yrs. of age.

PURPOSE

Anticavity
Anti-inflammatory

Use

Help protect against cavities and diminish inflammation.

Directions

Adults and children 2 yrs.& older: brush teeth thoroughly aftermeals or at least twice a day or use as directed by a dentist.
Do not swallow.
To minimize swallowing use a pea-sized amount in children under 6.
Supervise children's brushing until good habits are established.
Children under 2 yrs.: ask a dentist.

STORAGE AND HANDLING

Store in a dry and cool place.

Keep out of reach of children under 6 yrs. of age. If more than used for brushing is accidentally swallowed, get medical help or contact a Poison Control Center right away